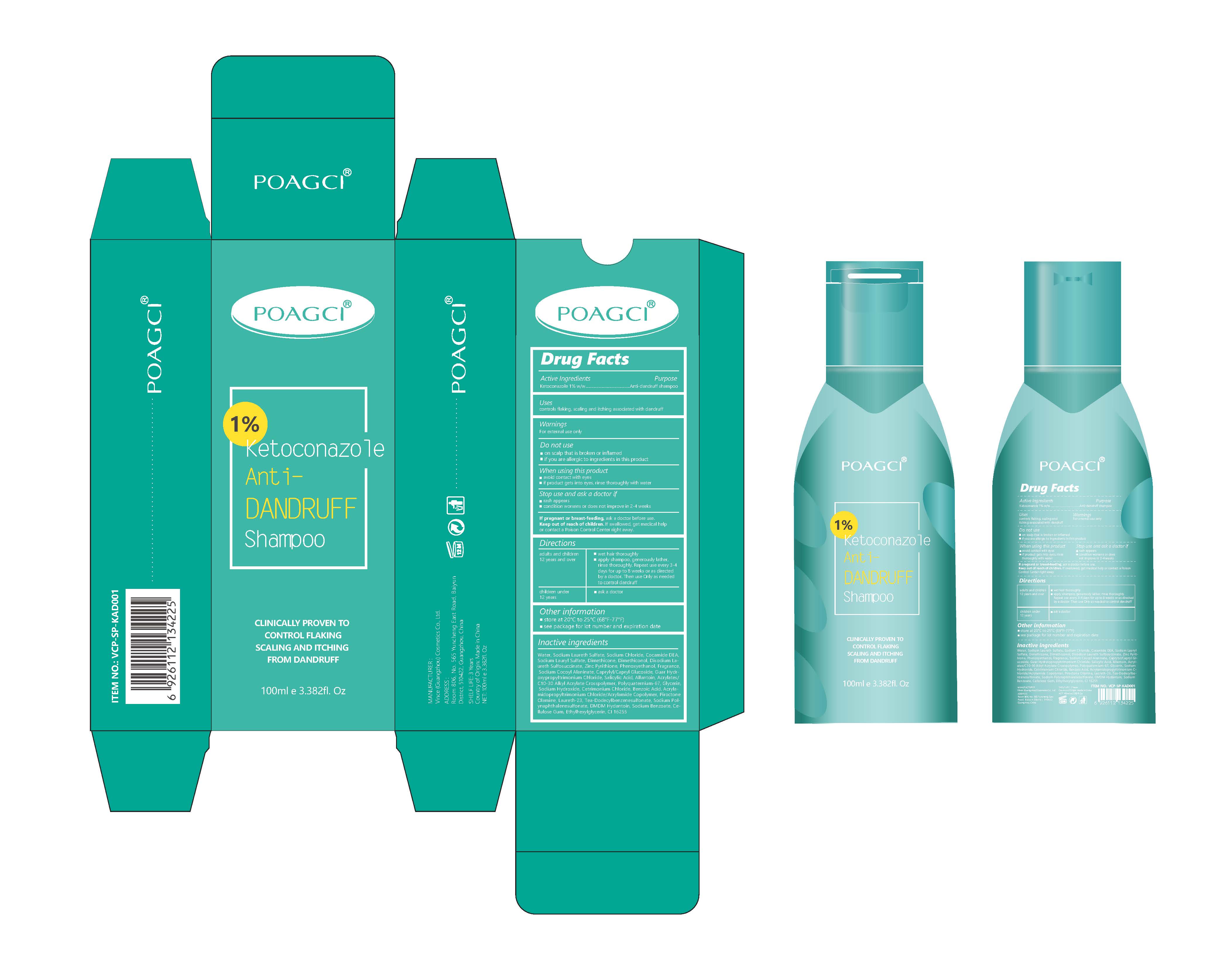 DRUG LABEL: POAGCI Ketoconazole VCP-KAD001
NDC: 84745-002 | Form: LIQUID
Manufacturer: Vince (Guangzhou) Cosmetics Co., Ltd.
Category: otc | Type: HUMAN OTC DRUG LABEL
Date: 20241011

ACTIVE INGREDIENTS: KETOCONAZOLE 1 g/100 mL
INACTIVE INGREDIENTS: PHENOXYETHANOL; SODIUM LAURETH SULFATE

Active Ingredients

Ketoconazole 1% w/w

Purpose

Anti-dandruff shampoo

Uses

controls flaking, scaling and itching associated with dandruff

Warnings

For external use only

Do not use

on scalp that is broken or inflamed
if you are allergic to ingredients in this produc

When using this product

avoid contact with eyes
if product gets into eyes, rinse thoroughly with water

Stop use and ask a doctor if

rash appears
condition worsens or does not improve in 2-4 weeks

If pregnant or breast-feeding,

ask a doctor before use.

Keep out of reach of children.

If swallowed, get medical help or contact a Poison Control Center right away.

adults and children 12 years and over

wet hair thoroughly
apply shampoo, generously lather, rinse thoroughly.
Repeat use every 3-4 days for up to 8 weeks or as directed by a doctor. Then use only as needed to control dandruf

children under 12 years

ask a doctor

Other information

store at 20°C to 25°C (68°F-77°F)
see package for lot number and expiration date

Inactive ingredients

Water, Sodium Laureth Sulfate, Sodium Chloride, Cocamide DEA, Sodium Lauryl Sulfate, Dimethicone, Dimethiconol, Disodium Laureth Sulfosuccinate, Zinc Pyrithione, Phenoxyethanol, Fragrance, Sodium Cocoyl Alaninate, Caprylyl/Capryl Glucoside, Guar Hydroxypropyltrimonium Chloride, Salicylic Acid, Allantoin, Acrylates/C10-30 Alkyl Acrylate Crosspolymer, Polyquaternium-67, Glycerin, Sodium Hydroxide, Cetrimonium Chloride, Benzoic Acid, Acrylamidopropyltrimonium Chloride/Acrylamide Copolymer, Piroctone Olamine, Laureth-23, Tea-Dodecylbenzenesulfonate, Sodium Polynaphthalenesulfonate, DMDM Hydantoin, Sodium Benzoate, Cellulose Gum, Ethylhexylglycerin, CI 16255